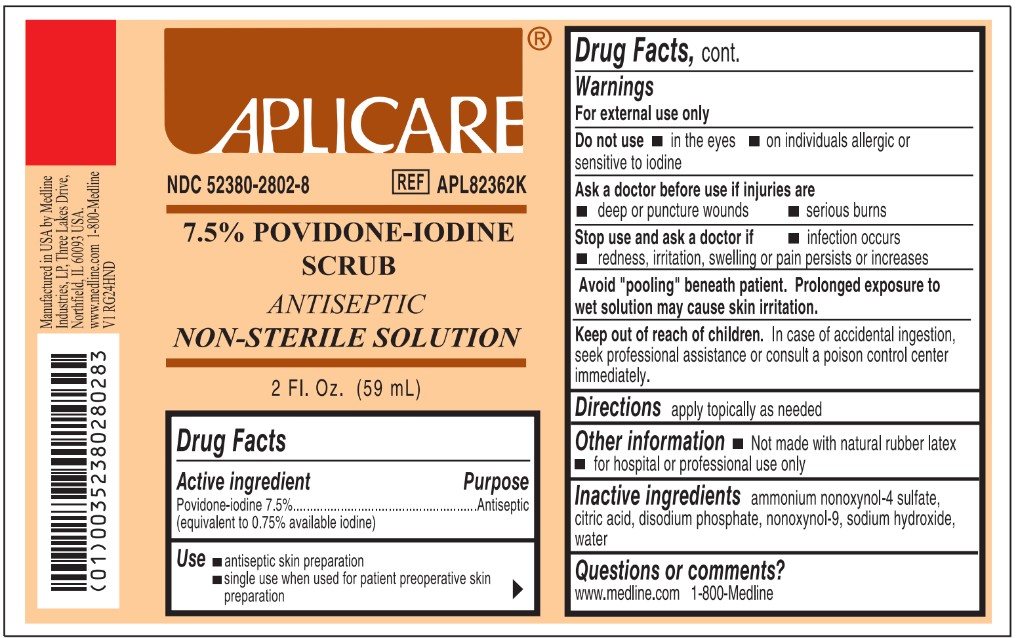 DRUG LABEL: Aplicare Povidone-iodine Scrub
NDC: 52380-2802 | Form: SOLUTION
Manufacturer: Aplicare Products, LLC
Category: otc | Type: HUMAN OTC DRUG LABEL
Date: 20250902

ACTIVE INGREDIENTS: POVIDONE-IODINE 7.5 mg/1 mL
INACTIVE INGREDIENTS: ANHYDROUS CITRIC ACID; SODIUM HYDROXIDE; NONOXYNOL-9; AMMONIUM NONOXYNOL-4 SULFATE; WATER; SODIUM PHOSPHATE, DIBASIC

2802 Aplicare Povidone-iodine Scrub

Active ingredient

Povidone Iodine 7.5%

Purpose

Antiseptic

Use

- • antiseptic skin preparation
- • single use when used for patient preoperative skin preparation and/or preinjection indications

Warnings

- For external use only
- Avoid "pooling" beneath patient. Prolonged exposure to wet solution may cause skin irritation.

Do not use

- • in the eyes
- • on individuals allergic or sensitive to iodine

Ask a doctor before use if injuries are

- • deep or puncture wounds
- • serious burns

Stop use and ask a doctor if

- • infection occurs
- • redness, irritation, or swelling or pain persists or increases

Keep out of reach of children.

In case of accidental ingestion, seek professional assistance or consult a poison control center immediately.

Directions

apply locally as needed

Other information

- • not made with natural rubber latex
- • for hospital or professional use only

Questions or comments?

www.medline.com 1-800-Medline

Inactive ingredients

ammonium nonoxynol-4 sulfate, citric acid, disodium phosphate, nonoxynol-9, sodium hydroxide, water

Manufacturing Information

Manufactured in USA by Medline Industries, LP,

Three Lakes Drive, Northfield, IL 60093 USA.

www.medline.com 1-800-Medline

REF: APL82362K

V1 RG24HND